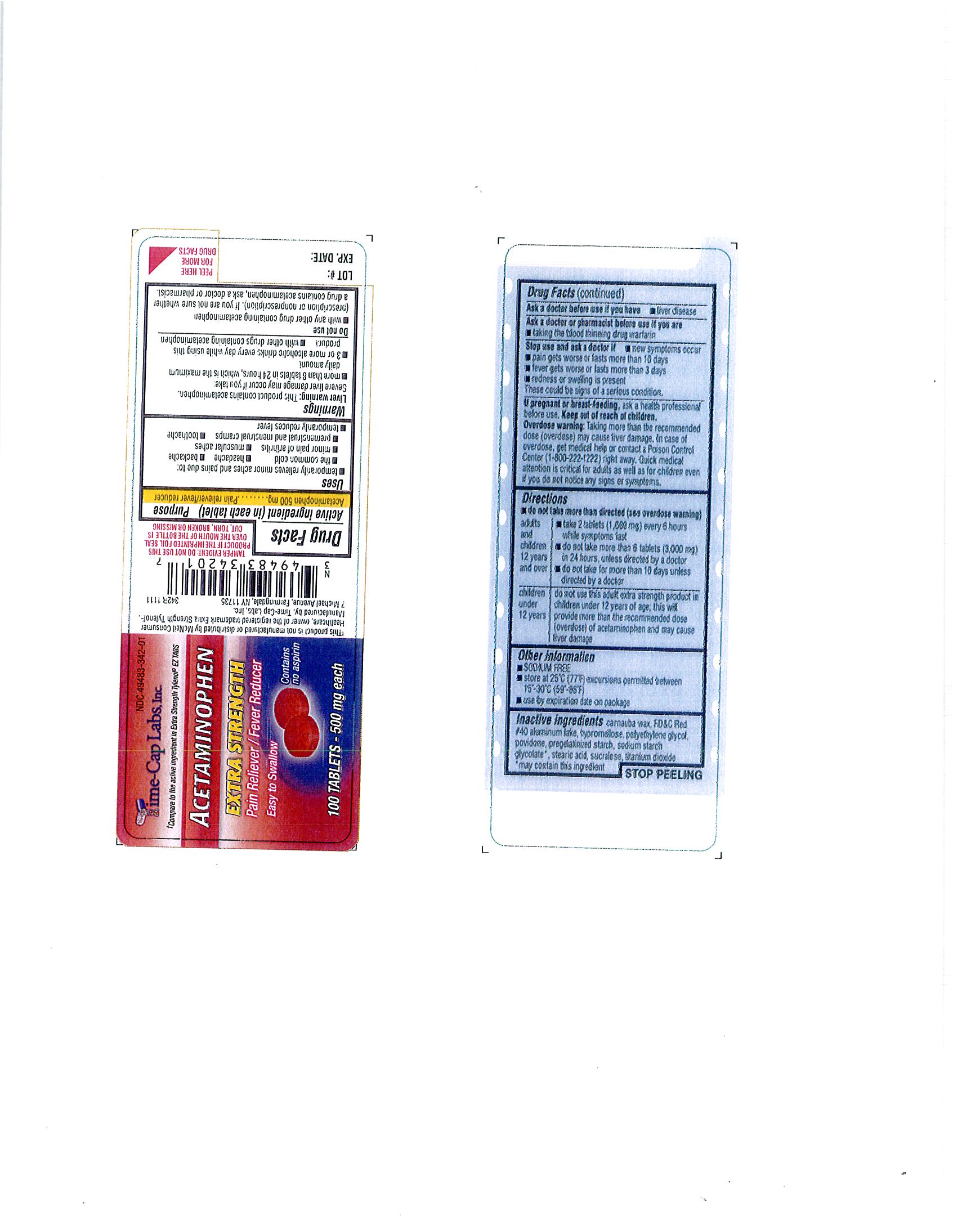 DRUG LABEL: ACETAMINOPHEN
NDC: 49483-342 | Form: TABLET, FILM COATED
Manufacturer: TIME CAP LABORATORIES, INC
Category: otc | Type: HUMAN OTC DRUG LABEL
Date: 20181217

ACTIVE INGREDIENTS: ACETAMINOPHEN 500 mg/1 1
INACTIVE INGREDIENTS: CARNAUBA WAX; FD&C RED NO. 40; HYPROMELLOSES; POLYETHYLENE GLYCOL 400; POLYETHYLENE GLYCOL 8000; POVIDONE; STARCH, CORN; SODIUM STARCH GLYCOLATE TYPE A POTATO; STEARIC ACID; SUCRALOSE; TITANIUM DIOXIDE

342R APAP

Active Ingredient: Each tablet contains Acetaminophen 500 mg

PURPOSE: Pain Reliever - fever reducer

KEEP OUT OF REACH OF CHILDREN

Keep Out of the Reach of Children: In case of overdose, get medical help or contact a Poison Control Center right away

INDICATIONS AND USAGE:

Pain Reliever – temporarily relieves minor aches and pains due to: the common cold, headache, backache, muscular aches, toothache, premenstrual and menstrual cramps, minor pain of arthritis. Temporarily reduces fever.

Warnings;
Liver warning: This product contains acetaminophen. Severe liver damage may occur if you take:more than 8 tablets in 24 hours, which is the maximum daily amount; 3 or more alcoholic drinks every day while using this product; with other drugs containing acetaminophen.

Overdose warning: Taking more than the recommended dose (0verdose) may cause liver damage. in case of overdose, get medical help or contact a Poison Control Center (1-800-222-1221) right way. Quick medical attention is critical for adults as well as children even if you do not notice any signs or symptoms.

DOSAGE AND ADMINISTRATION

Do not take more than directed (see overdosage warning)

Adults and children 12 years and over: take 2 tablets (1,000 mg) every 6 hours while symptoms last; do not take more than 6 tablets (3,000 mg) in 24 hours, unless directed by a doctor; do not take for more than 10 days unless directed by a doctor

Children under 12 years: Do not use this adult extra strength product in children under 12 years of age, this will provide more than the recommended dose (overdosage) of acetaminophen and may cause liver damage

INACTIVE INGREDIENT

CARNAUBA WAX, FD-C RED NO. 40 ALUMINUM LAKE, HYPROMELLOSE, POLYETHYLENE GLYCOL(PEG) 400, POLYETHYLENE GLYCOL (peg) 8000, POVIDONE, PREGELATINIZED STARCH, SODIUM STARCH GLYCOLATE**, STEARIC ACID, SUCRALOSE, TITANIUM DIOXIDE

** MAY CONTAIN THIS INGREDIENT